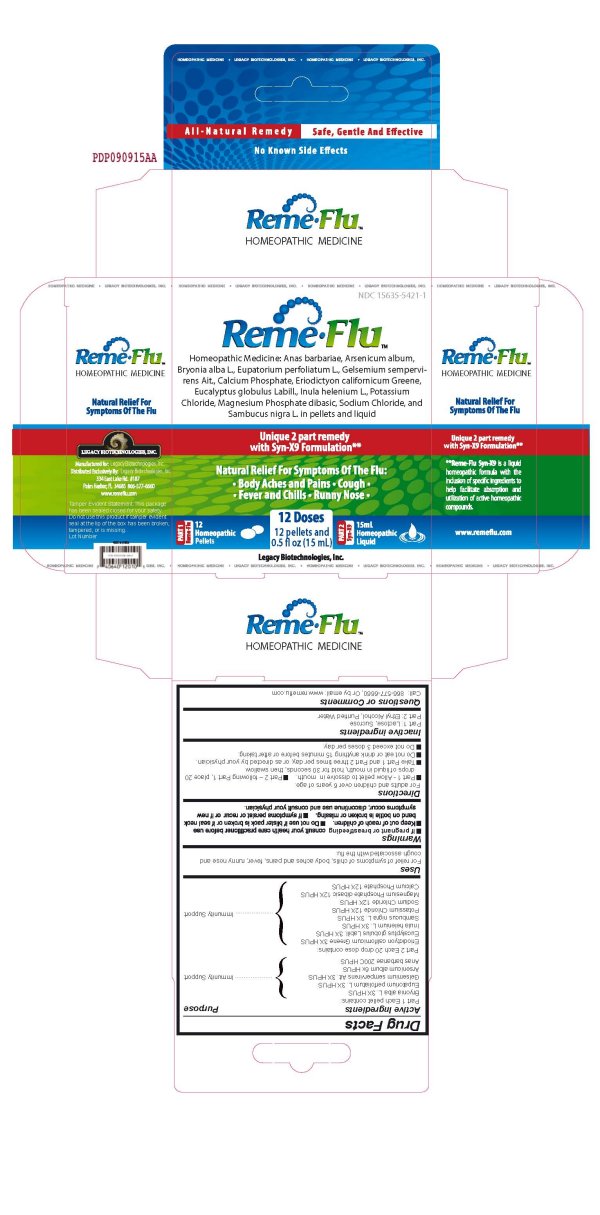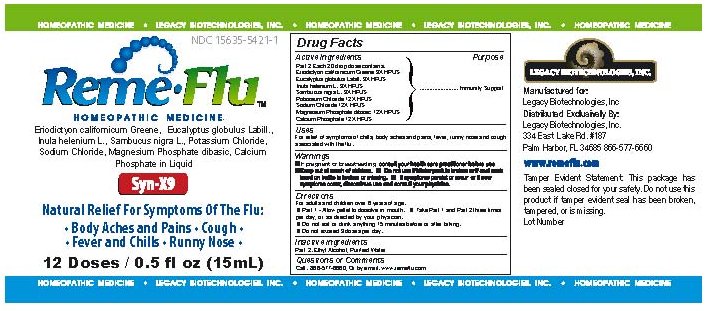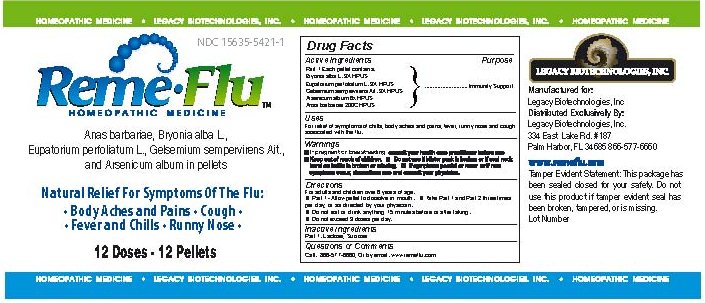 DRUG LABEL: Reme-Flu
NDC: 50107-100 | Form: KIT | Route: ORAL
Manufacturer: Legacy Biotechnologies Inc.
Category: homeopathic | Type: HUMAN OTC DRUG LABEL
Date: 20091222

ACTIVE INGREDIENTS: ERIODICTYON 3 [hp_X]/1 1; EUCALYPTUS GLOBULUS LEAF 3 [hp_X]/1 1; INULA 3 [hp_X]/1 1; SAMBUCUS NIGRA FLOWER 3 [hp_X]/1 1; POTASSIUM CHLORIDE 12 [hp_X]/1 1; SODIUM CHLORIDE 12 [hp_X]/1 1; MAGNESIUM PHOSPHATE 12 [hp_X]/1 1; TRIBASIC CALCIUM PHOSPHATE 12 [hp_X]/1 1; BRYONIA ALBA ROOT 3 [hp_X]/1 1; EUPATORIUM PERFOLIATUM FLOWERING TOP 3 [hp_X]/1 1; ARSENIC 3 [hp_X]/1 1; GELSEMIUM SEMPERVIRENS ROOT 6 [hp_X]/1 1
INACTIVE INGREDIENTS: ALCOHOL; WATER; LACTOSE; SUCROSE

Reme-Flu Homeopathic Medicine

Active Ingredients Purpose

Part 2 Each 20 drop dose contains: Immunity Support

Eriodictyon californicum Greene 3X HPUS

Eucalptus globulus Labill 3X HPUS

Inula helenium L. 3X HPUS

Sambucus nigra L. 3X HPUS

Potassium Chloride 12X HPUS

Sodium Chloride 12X HPUS

Magnesium Phosphate dibasic 12X HPUS

Calcium Phosphate 12X HPUS

Active Ingredients Purpose

Part 1 Each pellet contains: Immunity Support

Bryonia alba L. 3X HPUS

Eupatorium perfoliatum L. 3X HPUS

Gelsemium sempervirens Ait. 3X HPUS

Arsenicum album 6X HPUS

Anas barbariae 200C HPUS

Uses

For relief of symptoms of chills, body aches and pains, fever, runny nose and cough associated with the flu.

Warnings

If pregnant or breastfeeding consult your health care practitioner before use

Keep out of reach of children. Do not use if blister pack is broken or if seal neck band on bottle is broken or missing.

If symptoms persist or recur or if new symptoms occur, discontinue use and consult your physician.

Directions

For adults and children over 6 years of age.

Part 1 - Allow pellet to dissolve in mouth.

Take Part 1 and Part 2 three times per day, or as directed by your physician.

Do not eat or drink anything 15 minutes before or after taking.

Do not exceed 3 doses per day.

Inactive Ingredients

Part 1 Lactose, Sucrose

Part 2 Ethyl Alcohol, Purified Water

Questions or Comments

Call 866-577-6660, Or by email www.remeflu.com

DESCRIPTION

Legacy Biotechnologies, Inc.

Manufactured for:

Legacy Biotechnologies, Inc.

Distributed Exclusively By:

Legacy Biotechnologies, Inc.

334 East Lake Rd Number 187

Palm Harbor, FL 34685 866-577-6660

www.remeflu.com
Tamper Evident Statement: This package has
been sealed closed for your safety. Do not use this product if tamper evident
seal has been broken, tampered or is missing.

PACKAGE LABEL

Reme-Flu

Homeopathic Medicine

Anas barbariae, Bryonia alba L.,

Eupatorium perfoliatum L., Gelsemium sempervirens Ait.,

and Arsenicum album in pellets

Natural Relief For Symptoms Of The Flu:
Body Aches and Pains
Cough
Fever and Chills
Runny Nose
12 Doses - 12 Pellets

PACKAGE LABEL

Reme-Flu

Homeopathic Medicine

Eriodictyon californicum Greene, Eucalptus globulus Labill.,

Inula helenium L., Sambucus nigra L., Potassium Chloride,

Sodium Chloride, Magnesium Phosphate dibasic,

Calcium Phosphate in Liquid

Syn-X9

Natural Relief For Symptoms Of The Flu:

Body Aches and Pains

Cough

Fever and Chills

Runny Nose

12 Doses / 0.5 fl oz (15mL)